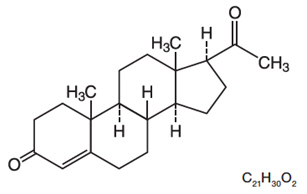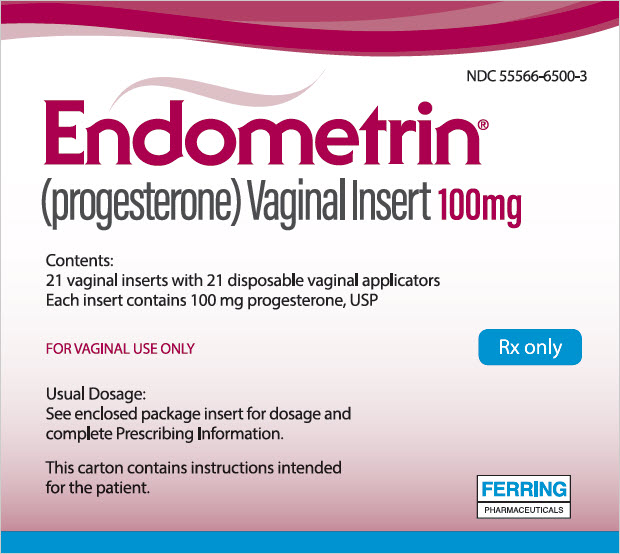 DRUG LABEL: ENDOMETRIN
NDC: 55566-6500 | Form: INSERT
Manufacturer: Ferring Pharmaceuticals Inc.
Category: prescription | Type: HUMAN PRESCRIPTION DRUG LABEL
Date: 20260224

ACTIVE INGREDIENTS: PROGESTERONE 100 mg/1 1
INACTIVE INGREDIENTS: LACTOSE MONOHYDRATE; POVIDONE K30; ADIPIC ACID; SODIUM BICARBONATE; SODIUM LAURYL SULFATE; MAGNESIUM STEARATE; STARCH, CORN; SILICON DIOXIDE

HIGHLIGHTS OF PRESCRIBING INFORMATION

These highlights do not include all the information needed to use ENDOMETRIN safely and effectively.
See full prescribing information for ENDOMETRIN.
ENDOMETRIN ® (progesterone)
Vaginal Insert 100 mg
Initial U.S. Approval: 2007

1 INDICATIONS AND USAGE

ENDOMETRIN® is a progesterone indicated to support embryo implantation and early pregnancy by supplementation of corpus luteal function as part of an Assisted Reproductive Technology (ART) treatment program for infertile women. (1)

2 DOSAGE AND ADMINISTRATION

The dose of ENDOMETRIN is 100 mg administered vaginally two or three times daily starting the day after oocyte retrieval and continuing for up to 10 weeks total duration. Efficacy in women 35 years of age and older has not been clearly established. The appropriate dose of ENDOMETRIN in this age group has not been determined. (2.1)

3 DOSAGE FORMS AND STRENGTHS

- 100 mg vaginal insert (3)

4 CONTRAINDICATIONS

- Previous allergic reactions to progesterone or any of the ingredients of ENDOMETRIN Vaginal Insert (4)
- Undiagnosed vaginal bleeding (4)
- Known missed abortion or ectopic pregnancy (4)
- Liver disease (4)
- Known or suspected malignancy of the breast or genital organs (4)
- Active arterial or venous thromboembolism or severe thrombophlebitis, or a history of these events (4)

5 WARNINGS AND PRECAUTIONS

- Life-threatening arterial or venous thromboembolic disorders may occur during hormone treatment, including treatment with ENDOMETRIN. Discontinue ENDOMETRIN if any of these are suspected. (5.1)
- Observe patients with a history of depression closely. Consider discontinuation if symptoms worsen. (5.2)
- ENDOMETRIN is not recommended for use with other vaginal products (such as antifungal products) as this may alter progesterone release and absorption from the vaginal insert. (5.3)

6 ADVERSE REACTIONS

The most common adverse reactions reported (greater than 2%) were post-oocyte retrieval pain, abdominal pain, nausea, and ovarian hyperstimulation syndrome. (6)

This leaflet summarizes the most important information about ENDOMETRIN. To report SUSPECTED ADVERSE REACTIONS, contact Ferring Pharmaceuticals Inc. at 1-888-FERRING (1-888-337-7464) or FDA at 1-800-FDA-1088 or www.fda.gov/medwatch.

FULL PRESCRIBING INFORMATION

1 INDICATIONS AND USAGE

ENDOMETRIN® (progesterone) is indicated to support embryo implantation and early pregnancy by supplementation of corpus luteal function as part of an Assisted Reproductive Technology (ART) treatment program for infertile women.

2 DOSAGE AND ADMINISTRATION

2.1 General Dosing Information

The dose of ENDOMETRIN is 100 mg administered vaginally two or three times daily starting the day after oocyte retrieval and continuing for up to 10 weeks total duration. Efficacy in women 35 years of age and older has not been clearly established. The appropriate dose of ENDOMETRIN in this age group has not been determined.

3 DOSAGE FORMS AND STRENGTHS

100 mg vaginal insert is a white to off-white oblong-shaped tablet debossed with "FPI" on one side and "100" on the other side.

4 CONTRAINDICATIONS

ENDOMETRIN is contraindicated in individuals with any of the following conditions:

- Previous allergic reactions to progesterone or any of the ingredients of ENDOMETRIN [see Description (11)]
- Undiagnosed vaginal bleeding
- Known missed abortion or ectopic pregnancy
- Liver disease
- Known or suspected malignancy of the breast or genital organs
- Active arterial or venous thromboembolism or severe thrombophlebitis, or a history of these events

5 WARNINGS AND PRECAUTIONS

5.1 Cardiovascular or Cerebrovascular Disorders

The physician should be alert to earliest signs of myocardial infarction, cerebrovascular disorders, arterial or venous thromboembolism (venous thromboembolism or pulmonary embolism), thrombophlebitis, or retinal thrombosis. ENDOMETRIN should be discontinued if any of these are suspected.

5.2 Depression

Patients with a history of depression need to be closely observed. Consider discontinuation if symptoms worsen.

5.3 Use of Other Vaginal Products

ENDOMETRIN should not be recommended for use with other vaginal products (such as antifungal products) as this may alter progesterone release and absorption from the vaginal insert [see Drug Interactions (7)].

6 ADVERSE REACTIONS

6.1 Clinical Studies Experience

Because clinical trials are conducted under widely varying conditions, adverse reaction rates observed in the clinical trials of a drug cannot be directly compared to rates in the clinical trials of another drug and may not reflect the rates observed in practice.

The safety data reflect exposure to ENDOMETRIN in 808 infertile women (74.9% White, 10.3% Hispanic, 5.4% Black, 5% Asian, and 4.6% Other) in a single Assisted Reproductive Technology 10 week clinical study conducted in the U.S. ENDOMETRIN was studied at doses of 100 mg twice daily and 100 mg three times daily. The adverse reactions that occurred at a rate greater than or equal to 2% in either ENDOMETRIN group are summarized in Table 1.

Table 1: Number and Frequency of Reported Adverse Reactions in Women Treated with ENDOMETRIN in an Assisted Reproductive Technology Study
Body System | ENDOMETRIN 100 mg twice daily (N=404) | ENDOMETRIN 100 mg three times daily (N=404)
Preferred Term | ENDOMETRIN 100 mg twice daily (N=404) | ENDOMETRIN 100 mg three times daily (N=404)
Gastrointestinal Disorders
Abdominal pain | 50 (12%) | 50 (12%)
Nausea | 32 (8%) | 29 (7%)
Abdominal distension | 18 (4%) | 17 (4%)
Constipation | 9 (2%) | 14 (3%)
Vomiting | 13 (3%) | 9 (2%)
General Disorders and Administration Site Conditions
Fatigue | 7 (2%) | 12 (3%)
Infections and Infestations
Urinary tract infection | 9 (2%) | 4 (1%)
Injury, Poisoning and Procedural Complications
Post-oocyte retrieval pain | 115 (28%) | 102 (25%)
Nervous System Disorders
Headache | 15 (4%) | 13 (3%)
Reproductive System and Breast Disorders
Ovarian hyperstimulation syndrome | 30 (7%) | 27 (7%)
Uterine spasm | 15 (4%) | 11 (3%)
Vaginal bleeding | 13 (3%) | 14 (3%)

Other less common reported adverse reactions included vaginal irritation, itching, burning, discomfort, urticaria, and peripheral edema.

6.2 Expected Adverse Reaction Profile Seen with Progesterone

ENDOMETRIN is also expected to have adverse reactions similar to other drugs containing progesterone that may include breast tenderness, bloating, mood swings, irritability, and drowsiness.

7 DRUG INTERACTIONS

No formal drug-drug interaction studies have been conducted for ENDOMETRIN. Drugs known to induce the hepatic cytochrome-P450-3A4 system (such as rifampin, carbamazepine) may increase the elimination of progesterone.

The effect of concomitant vaginal products on the exposure of progesterone from ENDOMETRIN has not been assessed. ENDOMETRIN is not recommended for use with other vaginal products (such as antifungal products) as this may alter progesterone release and absorption from the vaginal insert [see Warnings and Precautions (5.3)].

8 USE IN SPECIFIC POPULATIONS

8.1 Pregnancy

ENDOMETRIN has been used to support embryo implantation and maintain clinical pregnancy in one clinical study. The live birth outcomes of these pregnancies were as follows:

- Among the 404 subjects treated with ENDOMETRIN twice daily, 143 subjects had live births consisting of 85 singletons, 56 twins, and 2 triplets. In this treatment group, 13 subjects had a spontaneous abortion, 1 subject had an ectopic pregnancy, and 7 subjects reported fetal birth defects (3.4% based on 203 livebirths).
- Among the 404 subjects treated with ENDOMETRIN three times daily, 155 subjects had livebirths consisting of 91 singletons, 60 twins, and 4 triplets. In this treatment group, 22 subjects had a spontaneous abortion, 4 subjects had an ectopic pregnancy, and 7 subjects reported fetal birth defects (3.1% based on 223 livebirths).

Birth defects reported in the ENDOMETRIN twice daily group included: one fetus with a cleft palate and intrauterine growth retardation, one fetus with spina bifida, three fetuses with congenital heart defects, one fetus with an umbilical hernia, and one fetus with an intestinal anomaly.

Birth defects reported in the ENDOMETRIN three times daily group included: one fetus with an esophageal fistula, one fetus with hypospadias and an underdeveloped right ear, one fetus with Down Syndrome and an atrial septal defect, one fetus with congenital heart anomalies, one fetus with DiGeorge's syndrome, one fetus with a hand deformity, and one fetus with cleft palate.

For additional information on the pharmacology of ENDOMETRIN and pregnancy outcome information [ see Clinical Pharmacology (12) and Clinical Studies Sections (14)].

8.3 Nursing Mothers

Detectable amounts of progesterone have been identified in the milk of nursing mothers. The effect of this on the nursing infant has not been determined.

8.4 Pediatric Use

This drug is not intended for pediatric use and no clinical data have been collected in children. Therefore, the safety and effectiveness of ENDOMETRIN in pediatric patients have not been established.

8.5 Geriatric Use

No clinical data have been collected in patients over age 65.

10 OVERDOSAGE

Treatment of overdosage consists of discontinuation of ENDOMETRIN together with institution of appropriate symptomatic and supportive care.

11 DESCRIPTION

ENDOMETRIN (progesterone) Vaginal Insert contains micronized progesterone. ENDOMETRIN is supplied with polyethylene vaginal applicators.

The active ingredient, progesterone, is present in 100 mg amount along with other excipients. The chemical name for progesterone is pregn-4-ene-3,20-dione. It has an empirical formula of C21H30O2 and a molecular weight of 314.5. Progesterone exists in two polymorphic forms. The form used in ENDOMETRIN, the alpha-form, has a melting point of 127-131°C.

The structural formula is:

Each ENDOMETRIN Vaginal Insert delivers 100 mg of progesterone in a base containing lactose monohydrate, polyvinylpyrrolidone, adipic acid, sodium bicarbonate, sodium lauryl sulfate, magnesium stearate, pregelatinized starch, and colloidal silicon dioxide.

12 CLINICAL PHARMACOLOGY

12.1 Mechanism of Action

Progesterone is a naturally occurring steroid that is secreted by the ovary, placenta, and adrenal gland. In the presence of adequate estrogen, progesterone transforms a proliferative endometrium into a secretory endometrium. Progesterone is necessary to increase endometrial receptivity for implantation of an embryo. Once an embryo is implanted, progesterone acts to maintain a pregnancy.

12.3 Pharmacokinetics

Absorption

Progesterone serum concentrations increased following the administration of the ENDOMETRIN Vaginal Insert in 12 healthy pre-menopausal females. On single dosing, the mean Cmax was 17.0 ng/mL in the ENDOMETRIN twice daily group and 19.8 ng/mL in the ENDOMETRIN three times daily group. On multiple dosing, steady-state concentrations were attained within approximately 1 day after initiation of treatment with ENDOMETRIN. Both ENDOMETRIN regimens provided average serum concentrations of progesterone exceeding 10 ng/mL on Day 5. The pharmacokinetic results are summarized in Table 2.

Table 2: Mean (±Standard Deviation) Serum Progesterone Pharmacokinetic Parameters
Pharmacokinetic Parameter (unit) | ENDOMETRIN 100 mg twice daily (N=6) | ENDOMETRIN 100 mg three times daily (N=6)
Single Dosing
Cmax (ng/mL) | 17.0 ± 6.5 | 19.8 ± 7.2
Tmax (hr) | 24.0 ± 0.0 | 17.3 ± 7.4
AUC0-24 (ng∙hr/mL) | 217 ± 113 | 284 ± 143
Day 5 of Multiple Dosing
Cmax (ng/mL) | 18.5 ± 5.5 | 24.1 ± 5.6
Tmax (hr) | 18.0 ± 9.4 | 18.0 ± 9.4
Cmin (ng/mL) | 8.9 ± 4.5 | 10.9 ± 6.7
Cavg (ng/ml) | 14.0 ± 4.8 | 15.9 ± 4.3
AUC0-24 (ng∙hr/mL) | 327 ± 127 | 436 ± 106
Cmax Maximum progesterone serum concentration.
Tmax Time to maximum progesterone serum concentration.
Cavg Average progesterone serum concentration.
AUC0-24 Area under the drug concentration versus time curve from 0-24 hours post dose.
Cmin Minimum progesterone serum concentration.

Distribution

Progesterone is approximately 96% to 99% bound to serum proteins, primarily to serum albumin and corticosteroid binding globulin.

Metabolism

Progesterone is metabolized primarily by the liver, largely to pregnanediols and pregnanolones. Pregnanediols and pregnanolones are conjugated in the liver to glucuronide and sulfate metabolites. Progesterone metabolites that are excreted in the bile may be deconjugated and may be further metabolized in the gut via reduction, dehydroxylation, and epimerization.

Excretion

Progesterone undergoes renal and biliary elimination. Following injection of labeled progesterone, 50-60% of the excretion of metabolites occurs via the kidney; approximately 10% occurs via the bile and feces. Overall recovery of the labeled material accounts for 70% of an administered dose. Only a small portion of unchanged progesterone is excreted in the bile.

13 NONCLINICAL TOXICOLOGY

13.1 Carcinogenesis, Mutagenesis, Impairment of Fertility

Nonclinical toxicity studies to determine the potential of ENDOMETRIN to cause carcinogenicity or mutagenicity have not been performed. The effect of ENDOMETRIN on fertility has not been evaluated in animals.

14 CLINICAL STUDIES

14.1 Luteal Supplementation During Assisted Reproductive Treatment Study

A randomized, open-label, active-controlled study evaluated the efficacy of 10 weeks of treatment with two different daily dosing regimens of ENDOMETRIN (100 mg twice daily and 100 mg three times daily) for support of implantation and early pregnancy in infertile women participating in an Assisted Reproductive Technology treatment program. Efficacy was assessed on the endpoint of ongoing pregnancies, defined as the presence of at least one fetal heartbeat seen on ultrasound at 6 weeks post-embryo transfer. The study randomized to ENDOMETRIN 808 infertile women (74.9% White; 10.3% Hispanic, 5.4% Black, 5% Asian, and 4.6% Other) between 19 and 42 years of age (mean age 33) who had a body mass index <34 kg/m^2 at screening.

The ongoing pregnancy rates for subjects treated with both dosing regimens of ENDOMETRIN were non-inferior (lower bounds of the 95% confidence interval of the difference between ENDOMETRIN and the active comparator excluded a difference greater than 10%) to the ongoing pregnancy rate for subjects treated with the active comparator. The results of this study are shown in Table 3.

Table 3: Ongoing Pregnancy Rates [Ongoing pregnancy defined as the presence of at least one fetal heartbeat seen on ultrasound at 6 weeks post-embryo transfer.] in Patients Receiving ENDOMETRIN for Luteal Supplementation and Early Pregnancy While in an Assisted Reproductive Technology Treatment Program
 | ENDOMETRIN 100 mg twice daily | ENDOMETRIN 100 mg three times daily
Number of subjects | 404 | 404
Ongoing pregnancy: n (%) | 156 (39%) | 171 (42%)
95% Confidence Interval of pregnancy rate | [33.8, 43.6] | [37.5, 47.3]
Pregnancy rate percentage difference between ENDOMETRIN and comparator | -3.6% | 0.1%
95% Confidence Interval for difference vs comparator | [-10.3, 3.2] | [-6.7, 6.9]

Subjects participating in the study were stratified at randomization by age and ovarian reserve (as measured by serum FSH levels). The ongoing pregnancy rates for these subgroups are shown in Table 4.

Table 4: Ongoing Pregnancy Rates in Age- and Ovarian Reserve-Defined Subgroups Receiving ENDOMETRIN for Luteal Supplementation and Early Pregnancy While in an Assisted Reproductive Technology Treatment Program
 | ENDOMETRIN 100 mg twice daily | ENDOMETRIN 100 mg three times daily
Subjects age < 35 years (N) | 247 | 247
Ongoing pregnancy: n (%) | 111 (45%) | 117 (47%)
Pregnancy rate percentage difference between ENDOMETRIN and comparator | 0.5% | 2.9%
95% Confidence Interval for difference vs. comparator | [-8.3, 9.3] | [-5.9, 11.7]
Subjects 35-42 years of age (N) | 157 | 157
Ongoing pregnancy: n (%) | 45 (28%) | 54 (34%)
Pregnancy rate percentage difference between ENDOMETRIN and comparator | -10.1% | -4.4%
95% Confidence Interval for difference vs. comparator | [-20.3, 0.3] | [-14.9, 6.3]
Subjects with FSH < 10 IU/L (N) | 350 | 347
Ongoing pregnancy: n (%) | 140 (40%) | 150 (43%)
Pregnancy rate percentage difference between ENDOMETRIN and comparator | -2.0% | 1.2%
95% Confidence Interval for difference vs. comparator | [-9.3, 5.3] | [-6.1, 8.5]
Subjects with FSH between 10 and 15 IU/L (N) | 46 | 51
Ongoing pregnancy: n (%) | 16 (35%) | 20 (39%)
Pregnancy rate percentage difference between ENDOMETRIN and comparator | -12.2% | -7.7%
95% Confidence Interval for difference vs. comparator | [-31.0, 7.7] | [-26.6, 11.6]

In subjects under the age of 35 or with serum FSH levels less than 10 IU/L, results from both dosing regimens were non-inferior to the results from the comparator with respect to ongoing pregnancy rates. In women age 35 and older and in women with serum FSH levels between 10 and 15 IU/L, the results with respect to ongoing pregnancy rates for both dosing regimens of ENDOMETRIN did not reach the criteria for non-inferiority.

Subjects who became pregnant received study medication for a total of 10 weeks. Patients over 34 kg/m^2 were not studied. The efficacy of ENDOMETRIN in this patient group is unknown.

16 HOW SUPPLIED/STORAGE AND HANDLING

Each ENDOMETRIN Vaginal Insert is a white to off-white oblong-shaped insert debossed with "FPI" on one side and "100" on the other side. Each ENDOMETRIN (progesterone) Vaginal Insert, 100 mg, is packed individually in a sealed foil pouch. These pouches are available in cartons packed:

- 21 vaginal inserts with 21 disposable vaginal applicators (NDC 55566-6500-3)

STORAGE AND HANDLING

Store at 20 - 25°C (68 - 77°F); excursions permitted between 15 - 30°C (59 - 86°F).

17 PATIENT COUNSELING INFORMATION

See FDA-Approved Patient Labeling.

17.1 Vaginal Bleeding

Inform patients of the importance of reporting irregular vaginal bleeding to their doctor as soon as possible.

17.2 Common Adverse Reactions with Progesterone

Inform patients of the possible side effects of progesterone therapy such as headaches, breast tenderness, bloating, mood swings, irritability, and drowsiness.

17.3 Coadministration of Other Vaginal Products

Inform patients that ENDOMETRIN is not recommended for use with other vaginal products.

MANUFACTURED FOR:
FERRING PHARMACEUTICALS INC.
PARSIPPANY, NJ 07054

XXXXXXXXXX
Revised: 1/2025

PATIENT INFORMATION
ENDOMETRIN (en-doh-ME-trin)
(progesterone)
for vaginal insert

IMPORTANT: For Vaginal Use Only.
Read the patient information that comes with ENDOMETRIN ® (progesterone) before you start to use it and each time you get a refill. There may be new information. This leaflet does not take the place of talking with your doctor about your medical condition or treatment. Your doctor may do a physical exam before prescribing ENDOMETRIN.

What is ENDOMETRIN?
ENDOMETRIN is a vaginal insert that contains the hormone progesterone. ENDOMETRIN is for women who need extra progesterone while undergoing treatment in an Assisted Reproductive Technology (ART) program.
Progesterone is one of the hormones essential for helping you to become and to stay pregnant. If you are undergoing ART treatment, your doctor may prescribe ENDOMETRIN to provide the progesterone your body needs.

Who should not use ENDOMETRIN?
Do not use ENDOMETRIN if you:

- Are allergic to anything in ENDOMETRIN. See the end of this leaflet for a complete list of ingredients.
- Have unusual vaginal bleeding that has not been evaluated by a doctor.
- Currently have or have had liver problems or cancer of the breast or genital organs.
- Have or have had blood clots in the legs, lungs, eyes, or elsewhere in your body.

ENDOMETRIN may not be right for you. Before starting ENDOMETRIN, tell your doctor about all your health problems.

Tell your doctor about all the medicines you take including prescription and nonprescription medicines, vaginal products, vitamins, and herbal supplements.

Some medicines may affect ENDOMETRIN.

Know what medicines you take. Keep a list of your medicines to show to the doctor and pharmacist.

How should I use ENDOMETRIN?

- Use ENDOMETRIN exactly as prescribed. The usual dose of ENDOMETRIN is one insert placed in your vagina 2 to 3 times a day for up to a total of 10 weeks, unless your healthcare provider advises otherwise.
- Place an ENDOMETRIN insert in your vagina with the disposable applicator provided.

Follow the steps below:

- Unwrap the applicator. Do not use if the contents or packaging are visibly damaged.
- Put one insert in the space provided at the end of the applicator. The insert should fit snugly and not fall out.
- Place applicator with the insert into the vagina while you are standing, sitting, or when lying on your back with your knees bent. Gently place the thin end of the applicator well into the vagina.
- Push the plunger to release the insert.
- Remove the applicator and throw it away in the trash.

Other information for using ENDOMETRIN

- If you forget a dose of ENDOMETRIN, take the dose as soon as you remember, but do not use more than your daily dose.
- Call your doctor if you use too much ENDOMETRIN.
- Do not use any other vaginal products when you are using ENDOMETRIN.

What are the possible side effects of ENDOMETRIN?

Common side effects seen with ART and ENDOMETRIN included pelvic pain after surgery, abdominal pain, nausea, and swollen ovaries (ovarian hyperstimulation syndrome).

Other reported side effects included abdominal bloating, headache, urinary infections, uterine cramping, constipation, vomiting, tiredness, and vaginal bleeding.

Vaginal products with progesterone may also cause vaginal irritation, burning, and discharge.

Serious Risks of Progesterone

Progesterone can increase your chance of getting blood clots. Blood clots can be serious and lead to death.

Serious blood clots include those in the:

- legs (thrombophlebitis)
- lungs (pulmonary embolus)
- eyes (blindness)
- heart (heart attack)
- brain (stroke)

Call your doctor or get medical help right away if you have:

- persistent pain in the lower leg (calf)
- sudden shortness of breath
- coughing up blood
- sudden blindness, partial or complete
- severe chest pain
- sudden, severe headache, vomiting, dizziness, or fainting
- weakness in an arm or leg, or trouble speaking
- yellowing of the skin and/or white of the eyes indicating possible liver problem

Other risks of progesterone use include:

- headache
- breast tenderness
- bloating or fluid retention
- mood swings and depression
- irritability
- drowsiness

Call your doctor immediately if you have abnormal vaginal bleeding.

These are not all the side effects with ENDOMETRIN. Ask your doctor or pharmacist for more information.

How should I store ENDOMETRIN?

- Store ENDOMETRIN at room temperature, 20 - 25°C (68 - 77°F); excursions permitted between 15 - 30°C (59 - 86°F).
- Do not use ENDOMETRIN after the expiration date that is printed on the carton.
- Keep ENDOMETRIN and all medicines out of the reach of children.

General information about ENDOMETRIN

Medicines are sometimes prescribed for purposes other than those listed in a Patient Information Leaflet. Do not use ENDOMETRIN for a condition for which it was not prescribed. Do not give ENDOMETRIN to other women, even if they have the same condition as you do. It may harm them.

This leaflet summarizes the most important information about ENDOMETRIN. If you would like more information, talk with your doctor. You can ask your doctor or pharmacist for information about ENDOMETRIN that was written for healthcare professionals. For more information call Ferring Pharmaceuticals Inc. at 1-(888)-FERRING or 1-(888)-337-7464.

What are the ingredients in ENDOMETRIN?

Active Ingredient: progesterone

Inactive Ingredients: lactose monohydrate, polyvinylpyrrolidone, adipic acid, sodium bicarbonate, sodium lauryl sulfate, magnesium stearate, pregelatinized starch, and colloidal silicon dioxide

MANUFACTURED FOR:
FERRING PHARMACEUTICALS INC.
PARSIPPANY, NJ 07054

XXXXXXXXXX
Revised: 1/2025

PRINCIPAL DISPLAY PANEL - 100 mg Carton

NDC 55566-6500-3

Endometrin®
(progesterone) Vaginal Insert 100mg

Contents:
21 vaginal inserts with 21 disposable vaginal applicators
Each insert contains 100 mg progesterone, USP

FOR VAGINAL USE ONLY

Rx only

Usual Dosage:
See enclosed package insert for dosage and
complete Prescribing Information.

This carton contains instructions intended
for the patient.

FERRING
PHARMACEUTICALS